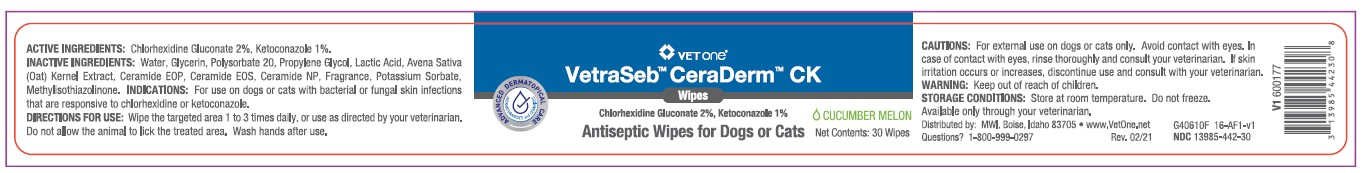 DRUG LABEL: VetraSeb CeraDerm
NDC: 13985-442 | Form: SWAB
Manufacturer: MWI/VETONE
Category: animal | Type: OTC ANIMAL DRUG LABEL
Date: 20210414

ACTIVE INGREDIENTS: CHLORHEXIDINE GLUCONATE 20 mg/1 1; KETOCONAZOLE 10 mg/1 1
INACTIVE INGREDIENTS: WATER; GLYCERIN; POLYSORBATE 20; PROPYLENE GLYCOL; LACTIC ACID; AVENANTHRAMIDES; CERAMIDE NP; POTASSIUM SORBATE; METHYLISOTHIAZOLINONE

DESCRIPTION

VetOne®

VetraSeb™ CeraDerm™ CK

Antiseptic Wipes for Dogs or Cats

ACTIVE INGREDIENTS: Chlorhexidine Gluconate 2%, Ketoconazole 1%.

INACTIVE INGREDIENTS: Water, Glycerin, Polysorbate 20, Propylene Glycol, Lactic Acid, Avena Sativa (Oat) Kernal Extract, Ceramide EOP, Ceramide EOS, Ceramide NP, Fragrance, Potassium Sorbate, Methylisothiazolinone.

INDICATIONS AND USAGE

INDICATIONS: For use on dogs or cats with bacterial or fungal skins infections that are responsive to chlorhexidine or ketoconazole.

DIRECTIONS FOR USE: Wipe the targeted area 1 to 3 times daily, or use as directed by your veterinarian. Do not allow the animal to lick the treated area. Wash hands after use.

WARNINGS AND PRECAUTIONS

CAUTIONS: For external use on dogs or cats only. Avoid contact with eyes. In case of contact with eyes, rinse thoroughly and consult your veterinarian. If skin irritation occurs or increases, discontinue use and consult with your veterinarian.

WARNING: Keep out of reach of children.

STORAGE AND HANDLING

STORAGE CONDITIONS: Store at room temperature. Do not freeze.

Available only through your veterinarian.

Distributed by: MWI, Boise, Idaho 83705 • www.VetOne.net

QUESTIONS? 1-800-999-029

PRINCIPAL DISPLAY PANEL - 30 Count Canister

VetOne®

VetraSeb™ CeraDerm™ CK

Wipes

Chlorhexidine Gluconate 2%, Ketoconazole 1%

CUCUMBER MELON

Antiseptic Wipes for Dogs or Cats

Net Contents: 30 Wipes